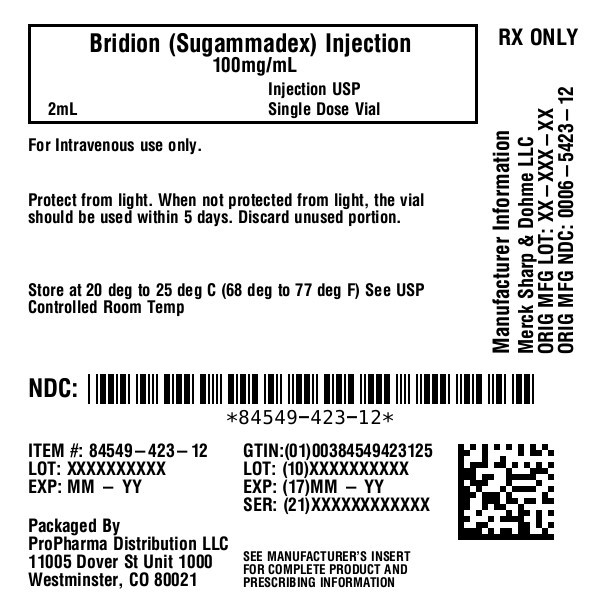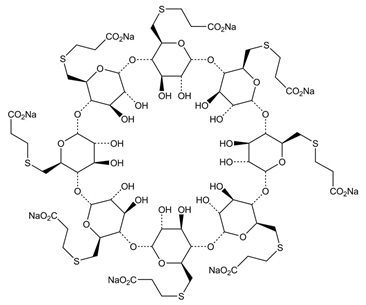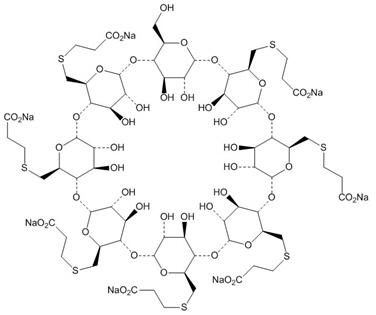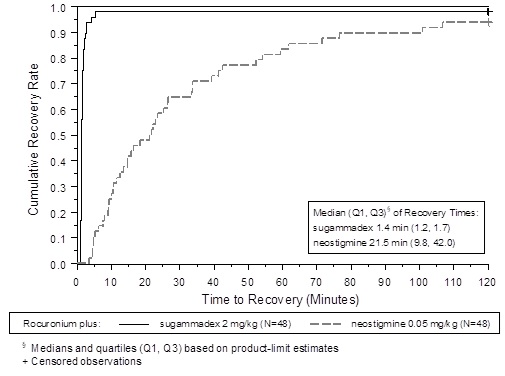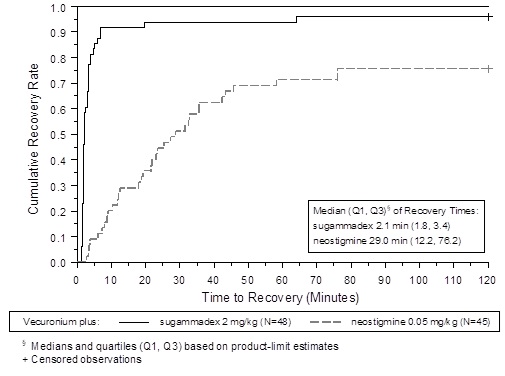 DRUG LABEL: BRIDION
NDC: 84549-423 | Form: INJECTION, SOLUTION
Manufacturer: ProPharma Distribution
Category: prescription | Type: HUMAN PRESCRIPTION DRUG LABEL
Date: 20251218

ACTIVE INGREDIENTS: SUGAMMADEX SODIUM 100 mg/1 mL
INACTIVE INGREDIENTS: HYDROCHLORIC ACID; SODIUM HYDROXIDE; WATER

HIGHLIGHTS OF PRESCRIBING INFORMATION

These highlights do not include all the information needed to use BRIDION safely and effectively. See full prescribing information for BRIDION.
BRIDION®(sugammadex) Injection, for intravenous use
Initial U.S. Approval: 2015

RECENT MAJOR CHANGES

Indication and Usage (1) | 12/2024

1 INDICATIONS AND USAGE

BRIDION is indicated for the reversal of neuromuscular blockade induced by rocuronium bromide and vecuronium bromide in adult and pediatric patients undergoing surgery. (1)

2 DOSAGE AND ADMINISTRATION

- Dosing is based on actual body weight (2.1)
- Monitor for twitch responses to determine the timing and dose for BRIDION administration. (2.1)
- Administer as a single bolus injection. (2.1)

For rocuronium and vecuronium:

- 4 mg/kg is recommended if spontaneous recovery of the twitch response has reached 1 to 2 post-tetanic counts (PTC) and there are no twitch responses to train-of-four (TOF) stimulation. (2.2)
- 2 mg/kg is recommended if spontaneous recovery has reached the reappearance of the second twitch in response to TOF stimulation. (2.2)

For rocuronium only:

- 16 mg/kg is recommended if there is a clinical need to reverse neuromuscular blockade soon (approximately 3 minutes) after administration of a single dose of 1.2 mg/kg of rocuronium. Immediate reversal in pediatric patients has not been studied. (2.2)

3 DOSAGE FORMS AND STRENGTHS

- 200 mg/2 mL (100 mg/mL) in a single-dose vial for bolus injection (3)
- 500 mg/5 mL (100 mg/mL) in a single-dose vial for bolus injection (3)

4 CONTRAINDICATIONS

Known hypersensitivity to sugammadex or any of its components. (4)

5 WARNINGS AND PRECAUTIONS

Anaphylaxis: Be prepared for hypersensitivity reactions (including anaphylactic reactions) and take necessary precautions. (5.1)

Marked Bradycardia: Cases of marked bradycardia, some of which have resulted in cardiac arrest, have been observed within minutes after administration. Monitor for hemodynamic changes and administer anticholinergic agents such as atropine if clinically significant bradycardia is observed. (5.2)

Respiratory Function Monitoring: Ventilatory support is mandatory until adequate spontaneous respiration is restored and the ability to maintain a patent airway is assured. Provide adequate ventilation if neuromuscular blockade persists after BRIDION or recurs following extubation. (5.3, 5.4)

Waiting Times for Re-Administration of Neuromuscular Blocking Agents: If re-administration of a neuromuscular blocking agent is required after reversal with BRIDION, waiting times should be based on the dose of BRIDION and the renal function of the patient. Consider use of a nonsteroidal neuromuscular blocking agent. (5.5)

6 ADVERSE REACTIONS

- Most common adverse reactions (reported in ≥10% of adult patients at a 2, 4, or 16 mg/kg BRIDION dose and higher than the placebo rate): vomiting, pain, nausea, hypotension, and headache. (6.1)
- Most common adverse reactions (reported in ≥10% of pediatric patients 2 to <17 years of age at BRIDION doses of 2 or 4 mg/kg) were pain, vomiting, and nausea. (6.1)
- Most common adverse reaction (reported in ≥10% of pediatric patients from birth to <2 years of age at BRIDION doses of 2 or 4 mg/kg) was procedural pain. (6.1)

To report SUSPECTED ADVERSE REACTIONS, contact Merck Sharp & Dohme LLC at 1-877-888-4231 or FDA at 1-800-FDA-1088 or www.fda.gov/medwatch.

7 DRUG INTERACTIONS

Toremifene: Concomitant use can delay recovery. (7.2)

Hormonal contraceptives: Patients must use an additional, non-hormonal method of contraception for 7 days following BRIDION administration. (5.6, 7.3)

8 USE IN SPECIFIC POPULATIONS

Severe Renal Impairment: Not recommended. (8.6)

FULL PRESCRIBING INFORMATION

1 INDICATIONS AND USAGE

BRIDION®is indicated for the reversal of neuromuscular blockade induced by rocuronium bromide and vecuronium bromide in adult and pediatric patients undergoing surgery.

2 DOSAGE AND ADMINISTRATION

2.1 Important Dosing and Administration Information

BRIDION dosing is based on actual body weight.

BRIDION (sugammadex) injection, for intravenous use, should be administered by trained healthcare providers familiar with the use, actions, characteristics, and complications of neuromuscular blocking agents (NMBA) and neuromuscular block reversal agents.

Doses and timing of BRIDION administration should be based on monitoring for twitch responses and the extent of spontaneous recovery that has occurred.

Administer BRIDION intravenously as a single bolus injection. The bolus injection may be given over 10 seconds, into an existing intravenous line. BRIDION has only been administered as a single bolus injection in clinical trials.

From the time of BRIDION administration until complete recovery of neuromuscular function, monitor the patient to assure adequate ventilation and maintenance of a patent airway. Satisfactory recovery should be determined through assessment of skeletal muscle tone and respiratory measurements in addition to the response to peripheral nerve stimulation.

The recommended dose of BRIDION does not depend on the anesthetic regimen.

Preparation of dilution for pediatric use:

BRIDION 100 mg/mL may be diluted to a concentration of 10 mg/mL, using 0.9% sodium chloride injection, USP, to increase the accuracy of dosing in the pediatric population.

- To prepare the required dose, aseptically transfer all the contents of the 2 mL vial of BRIDION 2-mL single-dose vials containing 200 mg sugammadex (100 mg/mL) to a bottle (or intravenous bag) containing 18 mL of 0.9% sodium chloride injection, to achieve a final concentration of 10 mg/mL sugammadex. The diluted solution should be used immediately.
- BRIDION injection is a single-dose sterile solution without preservatives. Discard any unused portion from the vial.

2.2 Recommended Dosing

BRIDION can be used to reverse different levels of rocuronium- or vecuronium-induced neuromuscular blockade.

For rocuronium and vecuronium:

- A dose of 4 mg/kg BRIDION is recommended if spontaneous recovery of the twitch response has reached 1 to 2 post-tetanic counts (PTC) and there are no twitch responses to train-of-four (TOF) stimulation following rocuronium- or vecuronium-induced neuromuscular blockade [see Warnings and Precautions (5.8)].
- A dose of 2 mg/kg BRIDION is recommended if spontaneous recovery has reached the reappearance of the second twitch (T2) in response to TOF stimulation following rocuronium- or vecuronium-induced neuromuscular blockade [see Warnings and Precautions (5.8)].

For rocuronium only:

- A dose of 16 mg/kg BRIDION is recommended if there is a clinical need to reverse neuromuscular blockade soon (approximately 3 minutes) after administration of a single dose of 1.2 mg/kg of rocuronium. The efficacy of the 16 mg/kg dose of BRIDION following administration of vecuronium has not been studied. Immediate reversal in pediatric patients has not been studied [see Clinical Studies (14.1)].

2.3 Drug Compatibility

May inject BRIDION into the intravenous line of a running infusion with the following intravenous solutions:

- 0.9% sodium chloride
- 5% dextrose
- 0.45% sodium chloride and 2.5% dextrose
- 5% dextrose in 0.9% sodium chloride
- isolyte P with 5% dextrose
- Ringer's lactate solution
- Ringer's solution

Ensure the infusion line is adequately flushed (e.g., with 0.9% sodium chloride) between administration of BRIDION and other drugs.

Do not mix BRIDION with other products except those listed above.

BRIDION is physically incompatible with verapamil, ondansetron, and ranitidine.

Visually inspect parenteral drug products for particulate matter and discoloration prior to administration, whenever the solution and container permit.

3 DOSAGE FORMS AND STRENGTHS

BRIDION (sugammadex) injection is a sterile, clear, colorless to slightly yellow-brown, non-pyrogenic aqueous solution intended for intravenous infusion. BRIDION is available as follows:

- 200 mg/2 mL (100 mg/mL) in a single-dose vial for bolus injection
- 500 mg/5 mL (100 mg/mL), in a single-dose vial for bolus injection

4 CONTRAINDICATIONS

BRIDION is contraindicated in patients with known hypersensitivity to sugammadex or any of its components. Hypersensitivity reactions that occurred varied from isolated skin reactions to serious systemic reactions (i.e., anaphylaxis, anaphylactic shock) and have occurred in patients with no prior exposure to sugammadex [see Warnings and Precautions (5.1), Adverse Reactions (6)] .

5 WARNINGS AND PRECAUTIONS

5.1 Anaphylaxis and Hypersensitivity

Clinicians should be prepared for the possibility of drug hypersensitivity reactions (including anaphylactic reactions) and take the necessary precautions [see Contraindications (4), Adverse Reactions (6.1)] .

Potentially serious hypersensitivity reactions, including anaphylaxis, have occurred in patients treated with BRIDION. The nature and frequency of anaphylaxis and hypersensitivity associated with BRIDION administration were evaluated in a randomized, double-blind, placebo-controlled, parallel-group, repeat-dose study in which 375 subjects were randomized to receive 3 doses of BRIDION IV with a 5-week washout period: 151 subjects received 4 mg/kg, 148 received 16 mg/kg and 76 received placebo. The frequency of anaphylaxis for the 299 healthy volunteers treated with intravenous BRIDION was 0.3% (n=1 in the BRIDION 16 mg/kg group on the first dose). Signs and symptoms included conjunctival edema, urticaria, erythema, swelling of the uvula and reduction in peak expiratory flow within 5 minutes of dose administration. The most common hypersensitivity adverse reactions reported were nausea, pruritus and urticaria and showed a dose response relationship, occurring more frequently in the 16 mg/kg group compared to the 4 mg/kg and placebo groups.

Anaphylaxis has also been reported in the post-marketing setting, including at doses less than 16 mg/kg. The most commonly described clinical features in reports of anaphylaxis were dermatologic symptoms (including urticaria, rash, erythema, flushing and skin eruption); and clinically important hypotension often requiring the use of vasopressors for circulatory support. In addition, prolonged hospitalization and/or the use of additional respiratory support until full recovery (re-intubation, prolonged intubation, manual or mechanical ventilation) have been noted in a number of the anaphylaxis reports.

5.2 Marked Bradycardia

Cases of marked bradycardia, some of which have resulted in cardiac arrest, have been observed within minutes after the administration of BRIDION [see Adverse Reactions (6.2)] . Patients should be closely monitored for hemodynamic changes during and after reversal of neuromuscular blockade. Treatment with anticholinergic agents, such as atropine, should be administered if clinically significant bradycardia is observed.

5.3 Respiratory Function Monitoring During Recovery

Ventilatory support is mandatory for patients until adequate spontaneous respiration is restored and the ability to maintain a patent airway is assured. Even if recovery from neuromuscular blockade is complete, other drugs used in the peri- and post-operative period could depress respiratory function and therefore ventilatory support might still be required.

Should neuromuscular blockade persist after BRIDION administration or recur following extubation, take appropriate steps to provide adequate ventilation.

5.4 Risk of Prolonged Neuromuscular Blockade

In clinical trials, a small number of patients experienced a delayed or minimal response to the administration of BRIDION [see Clinical Studies (14.1)] . Thus, it is important to monitor ventilation until recovery occurs.

5.5 Waiting Times for Re-Administration of Neuromuscular Blocking Agents for Intubation Following Reversal with BRIDION

A minimum waiting time is necessary before administration of a steroidal neuromuscular blocking agent after administration of BRIDION.

Table 1: Re-administration of Rocuronium or Vecuronium after Reversal (up to 4 mg/kg BRIDION)
Minimum Waiting Time | NMBA and Dose to be Administered
5 minutes | 1.2 mg/kg rocuronium
4 hours | 0.6 mg/kg rocuronium or 0.1 mg/kg vecuronium

When rocuronium 1.2 mg/kg is administered within 30 minutes after reversal with BRIDION, the onset of neuromuscular blockade may be delayed up to approximately 4 minutes and the duration of neuromuscular blockade may be shortened up to approximately 15 minutes.

The recommended waiting time in patients with mild or moderate renal impairment for re-use of 0.6 mg/kg rocuronium or 0.1 mg/kg vecuronium after reversal with up to 4 mg/kg BRIDION should be 24 hours. If a shorter waiting time is required, the rocuronium dose for a new neuromuscular blockade should be 1.2 mg/kg.

For re-administration of rocuronium or administration of vecuronium after reversal of rocuronium with 16 mg/kg BRIDION, a waiting time of 24 hours is suggested.

If neuromuscular blockade is required before the recommended waiting time has elapsed, use a nonsteroidal neuromuscular blocking agent. The onset of a depolarizing neuromuscular blocking agent might be slower than expected, because a substantial fraction of postjunctional nicotinic receptors can still be occupied by the neuromuscular blocking agent.

5.6 Interactions Potentially Affecting the Efficacy of Other Drugs

Due to the administration of BRIDION, certain drugs, including hormonal contraceptives, could become less effective due to a lowering of the (free) plasma concentrations. In this situation, consider the re-administration of the other drug, the administration of a therapeutically equivalent drug (preferably from a different chemical class), and/or non-pharmacological interventions as appropriate [see Drug Interactions (7.3)] .

5.7 Risk of Recurrence of Neuromuscular Blockade Due to Displacement Interactions

Recurrence of neuromuscular blockade may occur due to displacement of rocuronium or vecuronium from BRIDION by other drugs [see Drug Interactions (7.2)] . In this situation the patient may require mechanical ventilation. Administration of the drug which caused displacement should be stopped in case of an infusion. The risk of displacement reactions will be the highest in the time period equivalent to 3 times the half-life of BRIDION [see Clinical Pharmacology (12.3)] .

5.8 Risk of Recurrence of Neuromuscular Blockade with Lower Than Recommended Dosing

The use of lower than recommended doses of BRIDION may lead to an increased risk of recurrence of neuromuscular blockade after initial reversal and is not recommended [see Dosage and Administration (2.2), Adverse Reactions (6.1)] .

5.9 Risk of Recurrence of Neuromuscular Blockade Due to the Administration of Drugs that Potentiate Neuromuscular Blockade

When drugs which potentiate neuromuscular blockade are used in the post-operative phase, special attention should be paid to the possibility of recurrence of neuromuscular blockade. Refer to the package insert for rocuronium or vecuronium for a list of the specific drugs which potentiate neuromuscular blockade. In case recurrence of neuromuscular blockade is observed, the patient may require mechanical ventilation.

5.10 Risk of Coagulopathy and Bleeding

BRIDION doses up to 16 mg/kg were associated with increases in the coagulation parameters activated partial thromboplastin time (aPTT) and prothrombin time/international normalized ratio [PT(INR)] of up to 25% for up to 1 hour in healthy volunteers.

In patients undergoing major orthopedic surgery of the lower extremity who were concomitantly treated with heparin or low molecular weight heparin for thromboprophylaxis, increases in aPTT and PT(INR) of 5.5% and 3.0%, respectively, were observed in the hour following BRIDION 4 mg/kg administration. This clinical trial did not demonstrate an increased blood loss or anemia incidence with BRIDION compared with usual treatment. The rate of adjudicated bleeding events within 24 hours was 2.9% for sugammadex and 4.1% for usual care. The rate of post-operative anemia was 21% for sugammadex and 22% for usual care. The mean 24-hour drainage volume was 0.46 L for sugammadex and 0.48 L for usual care. The need for any post-operative transfusion was 37% for sugammadex and 39% for usual care.

In vitroexperiments demonstrated additional aPTT and PT(INR) prolongations for sugammadex in combination with vitamin K antagonists, unfractionated heparin, low molecular weight heparinoids, rivaroxaban, and dabigatran up to ~25% and ~50% at Cmaxlevels of sugammadex corresponding to 4 mg/kg and 16 mg/kg doses, respectively.

Since bleeding risk has been studied systematically with only heparin and low molecular weight heparin thromboprophylaxis and 4 mg/kg doses of sugammadex coagulation parameters should be carefully monitored in patients with known coagulopathies, being treated with therapeutic anticoagulation, receiving thromboprophylaxis drugs other than heparin and low molecular weight heparin, or receiving thromboprophylaxis drugs and who then receive a dose of 16 mg/kg sugammadex.

5.11 Renal Impairment

BRIDION is not recommended for use in patients with severe renal impairment, including those requiring dialysis [see Use in Specific Populations (8.6)] . With regard to the recommended waiting time for re-administration in patients with mild or moderate renal impairment, see Waiting Times for Re-Administration of Neuromuscular Blocking Agents for Intubation Following Reversal with BRIDION [see Warnings and Precautions (5.5)] .

5.12 Light Anesthesia

When neuromuscular blockade was reversed intentionally in the middle of anesthesia in clinical trials, e.g., when investigating urgent reversal, signs of light anesthesia were noted occasionally (movement, coughing, grimacing and suckling of the tracheal tube).

5.13 Reversal after Rocuronium or Vecuronium Administration in the ICU

BRIDION has not been studied for reversal following rocuronium or vecuronium administration in the ICU.

5.14 Reversal of Neuromuscular Blocking Agents Other Than Rocuronium or Vecuronium

Do not use BRIDION to reverse blockade induced by nonsteroidalneuromuscular blocking agents such as succinylcholine or benzylisoquinolinium compounds.

Do not use BRIDION to reverse neuromuscular blockade induced by steroidalneuromuscular blocking agents other than rocuronium or vecuronium.

6 ADVERSE REACTIONS

The following serious adverse reactions are described elsewhere in the labeling:

- Anaphylaxis and Hypersensitivity [see Contraindications (4), Warnings and Precautions (5.1)]
- Marked Bradycardia [see Warnings and Precautions (5.2)]

6.1 Clinical Trials Experience

Because clinical trials are conducted under widely varying conditions, adverse reaction rates observed in the clinical trials of a drug cannot be directly compared to rates in the clinical trials of another drug and may not reflect the rates observed in practice.

Adult Patients

The data described below reflect 2914 subjects exposed to 2, 4, or 16 mg/kg BRIDION and 544 to placebo in pooled Phase 1-3 studies. The population was 18 to 92 years old, 47% male and 53% female, 34% ASA (American Society of Anesthesiologists) Class 1, 51% ASA Class 2, and 14% ASA Class 3, and 82% Caucasian. Most subjects received a single dose of BRIDION 2 mg/kg or 4 mg/kg.

Adverse reactions reported in ≥10% of patients at a 2, 4, or 16 mg/kg BRIDION dose with a rate higher than the placebo rate are: vomiting, pain, nausea, hypotension, and headache.

All adverse reactions occurring in ≥2% of subjects treated with BRIDION and more often than placebo for adult subjects who received anesthesia and/or neuromuscular blocking agent in pooled Phase 1 to 3 studies are presented in Table 2.

Table 2: Percent of Subject Exposures in Pooled Phase 1 to 3 Studies with Adverse Reactions Incidence ≥2%
 | Sugammadex |  |  | Placebo
Body System Preferred Term | 2 mg/kg (N=895) n (%) | 4 mg/kg (N=1921) n (%) | 16 mg/kg (N=98) n (%) | (N=544) n (%)
Injury, poisoning and procedural complications
Incision site pain | 58 (6) | 106 (6) | 4 (4) | 6 (1)
Procedural complication | 13 (1) | 27 (1) | 8 (8) | 3 (1)
Airway complication of anesthesia | 11 (1) | 13 (1) | 9 (9) | 0
Anesthetic complication | 8 (1) | 14 (1) | 9 (9) | 1 (<1)
Wound hemorrhage | 5 (1) | 38 (2) | 0 | 8 (1)
Recurrence of neuromuscular blockade | 0 | 1 (<1) | 2 (2) | 0
Gastrointestinal disorders
Nausea [Combinations of preferred terms are as follows: Nausea includes preferred terms nausea and procedural nausea Vomiting includes preferred terms vomiting and procedural vomiting Abdominal pain includes preferred terms abdominal pain, abdominal pain upper, abdominal discomfort, abdominal pain lower, and epigastric discomfort Pain includes preferred terms pain and procedural pain Red blood cell count decreased includes preferred terms red blood cell count decreased, hemoglobin decreased, and hematocrit decreased Electrocardiogram QT interval abnormal includes preferred terms electrocardiogram QT interval abnormal and electrocardiogram QT interval prolonged Hypertension includes preferred terms hypertension, procedural hypertension, and blood pressure increased Hypotension includes preferred terms hypotension, procedural hypotension, and blood pressure decreased Tachycardia includes preferred terms tachycardia and heart rate increased Bradycardia includes preferred terms bradycardia and heart rate decreased] | 208 (23) | 503 (26) | 23 (23) | 127 (23)
Vomiting | 98 (11) | 236 (12) | 15 (15) | 57 (10)
Abdominal pain | 48 (5) | 68 (4) | 6 (6) | 17 (3)
Flatulence | 17 (2) | 51 (3) | 1 (1) | 10 (2)
Dry mouth | 9 (1) | 5 (<1) | 2 (2) | 0
General disorders and administration site conditions
Pain | 434 (48) | 993 (52) | 35 (36) | 207 (38)
Pyrexia | 77 (9) | 109 (6) | 5 (5) | 17 (3)
Chills | 30 (3) | 61 (3) | 7 (7) | 27 (5)
Nervous system disorders
Headache | 61 (7) | 99 (5) | 10 (10) | 42 (8)
Dizziness | 44 (5) | 67 (3) | 6 (6) | 13 (2)
Hypoesthesia | 12 (1) | 24 (1) | 3 (3) | 9 (2)
Respiratory, thoracic and mediastinal disorders
Oropharyngeal pain | 42 (5) | 66 (3) | 5 (5) | 27 (5)
Cough | 13 (1) | 49 (3) | 8 (8) | 11 (2)
Musculoskeletal and connective tissue disorders
Pain in extremity | 13 (1) | 35 (2) | 6 (6) | 15 (3)
Musculoskeletal pain | 16 (2) | 33 (2) | 1 (1) | 6 (1)
Myalgia | 5 (1) | 17 (1) | 2 (2) | 3 (1)
Psychiatric disorders
Insomnia | 20 (2) | 103 (5) | 5 (5) | 22 (4)
Anxiety | 14 (2) | 19 (1) | 3 (3) | 1 (<1)
Restlessness | 3 (<1) | 17 (1) | 2 (2) | 2 (<1)
Depression | 2 (<1) | 5 (<1) | 2 (2) | 0
Investigations
Red blood cell count decreased | 13 (1) | 34 (2) | 1 (1) | 2 (<1)
Electrocardiogram QT interval abnormal | 13 (1) | 7 (<1) | 6 (6) | 4 (1)
Blood creatine phosphokinase increased | 9 (1) | 14 (1) | 2 (2) | 1 (<1)
Vascular disorders
Hypertension | 48 (5) | 96 (5) | 9 (9) | 38 (7)
Hypotension | 33 (4) | 102 (5) | 13 (13) | 20 (4)
Skin and subcutaneous tissue disorders
Pruritus | 17 (2) | 50 (3) | 2 (2) | 9 (2)
Erythema | 5 (1) | 31 (2) | 0 | 6 (1)
Metabolism and nutrition disorders
Hypocalcemia | 15 (2) | 12 (1) | 0 | 4 (1)
Cardiac disorders
Tachycardia | 17 (2) | 29 (2) | 5 (5) | 4 (1)
Bradycardia | 9 (1) | 21 (1) | 5 (5) | 6 (1)
Surgical and medical procedures
Hysterectomy | 0 | 0 | 2 (2) | 0

Pediatric Patients

2 to <17 years of age

The safety of BRIDION has been assessed in a randomized, active-controlled study of pediatric patients 2 to <17 years of age, with 242 receiving treatment with BRIDION. Adverse events occurring in ≥5% of pediatric patients are presented in Table 3. The safety profile was generally consistent with that observed in adults.

Table 3: Pediatric Patients (2 to <17 years of age) with Adverse Events Incidence ≥5% in One or More Treatment Groups Up to 7 Days Post-Treatment
 | Sugammadex 2 mg/kg |  | Sugammadex 4 mg/kg
 | n | (%) | n | (%)
Subjects in population | 51 |  | 191
with one or more specific adverse events | 40 | (78) | 143 | (75)
with no specific adverse events | 11 | (22) | 48 | (25)
Cardiac disorders | 5 | (10) | 16 | (8)
Bradycardia [Combines preferred terms of bradycardia and sinus bradycardia Every subject is counted a single time for each applicable row and column. A system organ class or specific adverse event appears in this table only if its incidence in one or more of the columns meets the incidence criterion in the table title, after rounding.] | 5 | (10) | 13 | (7)
Eye disorders | 3 | (6) | 1 | (1)
Gastrointestinal disorders | 8 | (16) | 35 | (18)
Nausea | 1 | (2) | 12 | (6)
Vomiting | 4 | (8) | 20 | (10)
Injury, poisoning and procedural complications | 34 | (67) | 121 | (63)
Incision site pain | 3 | (6) | 6 | (3)
Procedural nausea | 4 | (8) | 9 | (5)
Procedural pain | 30 | (59) | 111 | (58)
Procedural vomiting | 3 | (6) | 5 | (3)

Birth to <2 years of age

The safety of BRIDION has been assessed in a randomized, double-blinded, active comparator-controlled study of pediatric patients from birth to <2 years of age, with 107 receiving treatment with BRIDION. Adverse events occurring in ≥5% of pediatric patients are presented in Table 4. The safety profile was generally consistent with that observed in pediatric patients from 2 to <17 years of age and adults.

Table 4: Pediatric Participants (Birth to <2 Years) with Specific Adverse Events Incidence ≥ 5% in One or More Treatment Groups Up to 7 Days Post-Treatment
 | Sugammadex 2 mg/kg |  | Sugammadex 4 mg/kg
 | n | (%) | n | (%)
Participants in population | 44 |  | 63
with one or more specific adverse events | 30 | (68.2) | 43 | (68.3)
with no specific adverse events | 14 | (31.8) | 20 | (31.7)
Cardiac disorders | 3 | (6.8) | 0 | (0.0)
Gastrointestinal disorders | 6 | (13.6) | 4 | (6.3)
Vomiting | 4 | (9.1) | 1 | (1.6)
General disorders and administration site conditions | 5 | (11.4) | 6 | (9.5)
Pyrexia | 3 | (6.8) | 3 | (4.8)
Infections and infestations | 3 | (6.8) | 0 | (0.0)
Injury, poisoning and procedural complications | 19 | (43.2) | 35 | (55.6)
Procedural pain | 18 | (40.9) | 34 | (54.0)
Procedural vomiting | 3 | (6.8) | 1 | (1.6)
Metabolism and nutrition disorders | 3 | (6.8) | 2 | (3.2)
Respiratory, thoracic and mediastinal disorders | 5 | (11.4) | 3 | (4.8)
Every participant is counted a single time for each applicable row and column.
A system organ class or specific adverse event appears in this table only if its incidence in one or more of the columns meets the incidence criterion in the table title, after rounding.

Anaphylaxis and Hypersensitivity

Hypersensitivity reactions, including anaphylaxis, have occurred in both premarketing clinical trials and in post-marketing spontaneous reports. In a dedicated hypersensitivity study in healthy volunteers, the frequency of anaphylaxis was 0.3% [see Warnings and Precautions (5.1)] . These reactions varied from isolated skin reactions to serious systemic reactions (i.e., anaphylaxis, anaphylactic shock) and have occurred in patients with no prior exposure to sugammadex.

Symptoms associated with these reactions can include: flushing, urticaria, erythematous rash, (severe) hypotension, tachycardia, swelling of tongue, swelling of pharynx, bronchospasm and pulmonary obstructive events. Severe hypersensitivity reactions can be fatal.

A randomized, double-blind study examined the incidence of drug hypersensitivity reactions in healthy volunteers given up to 3 doses of placebo (N=76), sugammadex 4 mg/kg (N=151) or sugammadex 16 mg/kg (N=148). Reports of suspected hypersensitivity were adjudicated by a blinded committee. The incidence of adjudicated hypersensitivity was 1%, 7% and 9% in the placebo, sugammadex 4 mg/kg and sugammadex 16 mg/kg groups, respectively. There were no reports of anaphylaxis after placebo or sugammadex 4 mg/kg. There was a single case of adjudicated anaphylaxis after the first dose of sugammadex 16 mg/kg. The frequency of anaphylaxis for the 299 healthy volunteers treated with intravenous sugammadex was 0.3%. There was no evidence of increased frequency or severity of hypersensitivity with repeat dosing.

In a previous study of similar design, there were three adjudicated cases of anaphylaxis, all after sugammadex 16 mg/kg (incidence 1% in the 298 healthy volunteers treated with sugammadex).

Recurrence of Neuromuscular Blockade

In clinical studies with subjects treated with rocuronium or vecuronium, where BRIDION was administered using a dose labeled for the depth of neuromuscular blockade (N=2022), an incidence of <1% was observed for recurrence of neuromuscular blockade as based on neuromuscular monitoring or clinical evidence [see Warnings and Precautions (5.8)] .

Bronchospasm

In one dedicated clinical trial and in post-marketing data, in patients with a history of pulmonary complications [see Use in Specific Populations (8.9)] , bronchospasm was reported as a possibly related adverse event.

6.2 Post-Marketing Experience

The following adverse reactions have been identified during post-approval use of BRIDION. Because these reactions are reported voluntarily from a population of uncertain size, it is not always possible to reliably estimate their frequency or establish a causal relationship to drug exposure.

Cardiac Disorders:Cases of marked bradycardia and bradycardia with cardiac arrest have been observed within minutes after administration of sugammadex [see Warnings and Precautions (5.2)] . Other cardiac rhythm abnormalities have included atrial fibrillation, atrioventricular block, cardiac/cardiorespiratory arrest, electrocardiographic (ECG) ST segment changes, supraventricular tachycardia/extrasystoles, tachycardia, ventricular fibrillation, and ventricular tachycardia. Anaphylaxis associated with ECG ST segment changes (elevation or depression) consistent with myocardial ischemia or coronary spasm has also been reported.

General Disorders and Administration Site Conditions:Cases of BRIDION not having the intended effect.

Immune System Disorders:Hypersensitivity events including anaphylactic shock, anaphylactic reaction, anaphylactoid reaction, and Type 1 hypersensitivity have been reported [see Warnings and Precautions (5.1)] .

Respiratory, Thoracic, and Mediastinal Disorders:Events of laryngospasm, dyspnea, wheezing, pulmonary edema, and respiratory arrest have been reported.

7 DRUG INTERACTIONS

7.1 Summary

The information reported in sections 7.2– 7.4is based on binding affinity between BRIDION and other drugs, preclinical experiments, clinical studies and simulations of a pharmacokinetic-pharmacodynamic (PK-PD) model. Based on these considerations, no clinically significant pharmacodynamic interactions with other drugs are expected, with the exception of toremifene and hormonal contraceptives.

7.2 Interactions Potentially Affecting the Efficacy of BRIDION

Toremifene

For toremifene, which has a relatively high binding affinity for sugammadex and for which relatively high plasma concentrations might be present, some displacement of vecuronium or rocuronium from the complex with BRIDION could occur. The recovery to TOF ratio to 0.9 could therefore be delayed in patients who have received toremifene on the same day of surgery.

7.3 Interaction Potentially Affecting the Efficacy of Hormonal Contraceptives

In vitrobinding studies indicate that BRIDION may bind to progestogen, thereby decreasing progestogen exposure. Therefore, the administration of a bolus dose of BRIDION is considered to be equivalent to missing dose(s) of oralcontraceptives containing an estrogen or progestogen. If an oral contraceptive is taken on the same day that BRIDION is administered, the patient must use an additional, non-hormonal contraceptive method or back-up method of contraception (such as condoms and spermicides) for the next 7 days.

In the case of non-oralhormonal contraceptives, the patient must use an additional, non-hormonal contraceptive method or back-up method of contraception (such as condoms and spermicides) for the next 7 days.

7.4 Interference with Laboratory Tests

BRIDION may interfere with the serum progesterone assay. Interference with this test was observed at sugammadex plasma concentrations of 100 mcg/mL, which may be observed for up to 30 minutes after a 16 mg/kg dose.

8 USE IN SPECIFIC POPULATIONS

8.1 Pregnancy

Risk Summary

There are no clinical trial data on BRIDION use in pregnant women to inform any drug-associated risks. The available data from the pharmacovigilance safety database and published literature on BRIDION use in pregnant women are insufficient to identify a drug-associated risk of major birth defects, miscarriage, or adverse maternal or fetal outcomes. In animal reproduction studies, there was no evidence of malformations following daily intravenous administration of sugammadex to rats and rabbits during organogenesis at exposures of up to 6 and 8 times, respectively, the maximum recommended human dose (MRHD) of 16 mg/kg. However, there was an increase in the incidence of incomplete ossification of the sternebra and reduced fetal body weights in the rabbit study at 8 times the MRHD, which is a dose level in which maternal toxicity was also observed. In a pre- and postnatal development study, sugammadex treatment resulted in an increase in early postnatal loss, which correlated with maternal behavior (increased incidence of pup cannibalism), at exposures equivalent to the MRHD and higher (see Data) . The background risk of major birth defects and miscarriage for the indicated population are unknown. However, the background risk in the U.S. general population of major birth defects is 2-4% and of miscarriage is 15-20% of clinically recognized pregnancies.

Data

Animal Data

In an embryofetal development study in rats, pregnant animals received daily intravenous administration of sugammadex at 0, 20, 100, and 500 mg/kg (0.2, 1, and 6 times the MRHD of 16 mg/kg/day, respectively, based on AUC comparison) during organogenesis (Gestational Days 6-17). No treatment-related maternal and embryofetal changes were observed.

In another embryofetal development study, pregnant New Zealand white rabbits received daily intravenous administration of sugammadex at 0, 20, 65, 200 mg/kg (0.6, 2, and 8 times the MRHD, respectively, based on AUC comparison) during organogenesis (Gestational Days 6-18). Fetal body weight decreases (10 and 14%, respectively) were observed in the offspring at maternal doses of 65 mg/kg and 200 mg/kg. In addition, incomplete ossification of sternebra, and unossified 1st metacarpal were noted at a maternal dose of 200 mg/kg/day. Maternal toxicity was also observed at 200 mg/kg. Considering the observed effects of sugammadex on bone [see Nonclinical Toxicology (13.2)] , it is possible that these findings may be attributable to drug. There was no evidence of malformations at any dose.

In a prenatal and postnatal development study, pregnant rats were administered sugammadex intravenously at 0, 30, 120, and 500 mg/kg (0.3, 1, and 6 times the MRHD, respectively, based on AUC comparison) from Gestational Day (GD) 6 to Postnatal Day (PND) 21 (corresponding to the beginning of organogenesis through parturition and subsequent pup weaning). Postnatal loss during PND 1-4 was noted across control litters and treated litters from dams receiving sugammadex as a result of pup cannibalization by dams. Overall incidence of affected litters was 2, 1, 4, and 3 litters, respectively, at 0, 30, 120, or 500 mg/kg/day. The reason for the increased cannibalization is not known. An effect of sugammadex on steroidal hormones and/or pheromones cannot be ruled out. In addition, there were no drug-related effects on parturition in rats during evaluations for prenatal or postnatal development.

8.2 Lactation

Risk Summary

No data are available regarding the presence of sugammadex in human milk, the effects of sugammadex on the breast fed infant, or the effects of sugammadex on milk production. However, sugammadex is present in rat milk (see Data) . The developmental and health benefits of breastfeeding should be considered along with the mother's clinical need for BRIDION and any potential adverse effects on the breastfed infant from BRIDION or from the underlying maternal condition.

Data

In a milk excretion study in rat dams following single intravenous dose of 20 mg/kg sugammadex on Postnatal Day 9, the maximum drug level was achieved at about 30 minutes after dosing with a ratio of milk to plasma level approximately 1:1. The oral exposure via milk did not induce effects on survival, body weight and physical or the behavioral developmental parameters monitored in rats in the prenatal and postnatal development studies [see Use in Specific Populations (8.1)] .

8.3 Females and Males of Reproductive Potential

Contraception

Upon administration of BRIDION, the efficacy of hormonal contraceptives may be reduced for up to 7 days. Advise female patients of reproductive potential using hormonal contraceptives to use an additional, non-hormonal contraceptive for the next 7 days following BRIDION administration [see Drug Interactions (7.3)] .

8.4 Pediatric Use

The safety and effectiveness of BRIDION for reversal of neuromuscular blockade induced by rocuronium bromide or vecuronium bromide have been established in pediatric patients from birth and older. Use of BRIDION in these age groups is supported by evidence from adequate and well-controlled studies of BRIDION [see Clinical Pharmacology (12.3)and Clinical Studies (14.1)]. In pediatric patients, the safety profile is generally consistent with that observed in adults [see Adverse Reactions (6.1)] .

Juvenile Animal Studies

In a bone deposition study, sugammadex concentrations were significantly higher in juvenile rats compared to adult rats (13% vs. 3% of the administered dose, respectively) following a single intravenous (IV) dose at 30 mg/kg (0.3 times the MRHD based on adult AUC comparison).

In a juvenile animal bone toxicity study, 7-day old rats were dosed intravenously once daily for 28 days with 0, 30, 120, and 500 mg/kg sugammadex (approximately 0.1, 0.6, and 3 times the MRHD, respectively, by adult AUC comparison). Sugammadex at 120 and 500 mg/kg decreased ulna and femur bone lengths by approximately 3%, which did not recover after an 8-week treatment-free period. Reversible whitish discoloration and disturbance of enamel formation were also observed in the incisors at these dose levels. In molars, this effect was only observed at 500 mg/kg. The no-observed-effect-level (NOEL) was 30 mg/kg.

In a second juvenile animal bone toxicity study, 7-day old rats were dosed once weekly for 8 weeks with 0, 7.5, 30, and 120 mg/kg (up to 1.2 times the MRHD of 16 mg/kg based on adult AUC comparison). No adverse effects on bone or teeth were noted.

8.5 Geriatric Use

BRIDION has been administered in a dedicated clinical study to a total 102 geriatric patients that compared the time to recovery from neuromuscular blockade induced by rocuronium (0.6 mg/kg) following administration of 2 mg/kg BRIDION given at the reappearance of T2in 65-74 year-olds (N=62) and ≥75 year-olds (N=40) compared with 18-64 year-olds (N=48). The median time to recovery of the TOF (T4/T1) ratio to 0.9 in 18-64 year-olds was 2.2 minutes; in 65-74 year-olds it was 2.5 minutes, and in ≥75 year-olds it was 3.6 minutes. For time to recovery from neuromuscular blockade induced by rocuronium following administration of 4 mg/kg BRIDION given at 1-2 PTCs, results across clinical trials revealed a median recovery of 2.5 minutes for geriatric patients (≥65 years, N=63) versus 2.0 minutes, for adults aged 18-64 years (N=359). Hence no dose adjustment is necessary in geriatric patients with normal organ function [see Dosage and Administration (2.2)] .

This drug is known to be substantially excreted by the kidney, and the risk of adverse reactions to this drug may be greater in patients with impaired renal function. Because elderly patients are more likely to have decreased renal function, care should be taken in dose selection, and it may be useful to monitor renal function [see Use in Specific Populations (8.6), Clinical Pharmacology (12.3)] .

8.6 Renal Impairment

This drug is known to be substantially excreted by the kidney. Effect of mild or moderate renal impairment (creatinine clearance ≥30 and ≤80 mL/min) on sugammadex PK and PD was obtained from a study in elderly patients [see Use in Specific Populations (8.5)] . Although clearance of drug decreased in elderly subjects with mild and moderate renal impairment, there was no significant difference in the ability of sugammadex to reverse the pharmacodynamic effect of rocuronium. Hence, no dosage adjustment is necessary for mild and moderate renal impairment. BRIDION is not recommended for use in patients with severe renal impairment (creatinine clearance <30 mL/min) due to insufficient safety information combined with the prolonged and increased overall exposure in these patients [see Warnings and Precautions (5.11), Clinical Pharmacology (12.3)] .

8.7 Hepatic Impairment

BRIDION is not metabolized nor excreted by the liver; therefore, dedicated trials in patients with hepatic impairment have not been conducted. Exercise caution when administering BRIDION to patients with hepatic impairment accompanied by coagulopathy or severe edema [see Warnings and Precautions (5.10, 5.14)] .

8.8 Cardiac Patients

One trial of 76 patients who were diagnosed with or have a history of cardiac disease (e.g., patients with ischemic heart disease, chronic heart failure, or arrhythmia) of primarily NYHA (New York Heart Association) Class II investigated time to recovery from neuromuscular blockade induced by rocuronium 0.6 mg/kg following administration of 2 mg/kg or 4 mg/kg BRIDION given at the reappearance of T2. The trial showed that the median time to recovery of the T4/T1ratio to 0.9 was 1.7 minutes and 1.3 minutes, respectively, in the 2 mg/kg and 4 mg/kg BRIDION dose groups. This is similar to the median values observed in the other trials; therefore, no dosage adjustment is necessary [see Dosage and Administration (2.2)] .

8.9 Pulmonary Patients

One trial of 77 patients who were diagnosed with or have a history of pulmonary complications investigated the time to recovery from neuromuscular blockade induced by rocuronium (0.6 mg/kg) following administration of 2 mg/kg or 4 mg/kg BRIDION given at the first signs of recovery (reappearance of T2). The trial showed that for these patients the median time to recovery of the T4/T1ratio to 0.9 was 2.1 minutes after a dose of 2 mg/kg BRIDION and 1.9 minutes after a dose of 4 mg/kg BRIDION. This is similar to the median values observed in the other trials; therefore, no dosage adjustment is necessary. [See Dosage and Administration (2.2), Adverse Reactions (6.1).]

8.10 Obese Patients with a BMI ≥40 kg/m^2

A trial of 188 obese patients, with a body mass index ≥40 kg/m^2, investigated the time to recovery from moderate or deep neuromuscular blockade induced by rocuronium or vecuronium. Patients received 2 mg/kg or 4 mg/kg BRIDION, as appropriate for level of block, dosed according to either actual body weight (ABW) or ideal body weight (IBW) in random, double-blinded fashion. Pooled across depth of block and neuromuscular blocking agent, the median time to recover to a train-of-four (TOF) ratio ≥0.9 in patients dosed by ABW (1.8 minutes) was statistically significantly faster compared to patients dosed by IBW (3.3 minutes).

The adverse reaction profile was generally similar to the profile in adult patients in pooled Phase 1 to 3 studies [see Adverse Reactions (6.1)] . No dosage adjustment is necessary [see Dosage and Administration (2.2)] .

8.11 American Society of Anesthesiologists Class 3 or 4 Patients

One trial of 331 patients who were assessed as ASA Class 3 or 4 investigated the incidence of treatment-emergent arrhythmias (sinus bradycardia, sinus tachycardia, or other cardiac arrhythmias) after administration of sugammadex.

In patients receiving sugammadex (2 mg/kg, 4 mg/kg, or 16 mg/kg), the number (%) of patients with treatment-emergent sinus bradycardia (up to 35 minutes post-administration of sugammadex) was 1/105 (1.0%) in the 2 mg/kg sugammadex treatment group, 2/107 (1.9%) in the 4 mg/kg sugammadex treatment group, and 5/68 (7.4%) in the 16 mg/kg sugammadex treatment group, compared to 4/51 (7.8%) in the neostigmine (50 µg/kg up to 5 mg maximum dose) + glycopyrrolate (10 µg/kg up to 1 mg maximum dose) treatment group. The number of patients with treatment-emergent sinus tachycardia (up to 35 minutes post-administration of sugammadex) was 7/105 (6.7%) in the 2 mg/kg sugammadex treatment group, 10/107 (9.3%) in the 4 mg/kg sugammadex treatment group, and 6/68 (8.8%) in the 16 mg/kg sugammadex treatment group, compared to 11/51 (21.6%) in the neostigmine + glycopyrrolate treatment group. The number of other treatment-emergent arrhythmias (up to 35 minutes post administration of sugammadex) was 1/105 (1.0%) in the 2 mg/kg sugammadex treatment group, 0/107 (0%) in the 4 mg/kg sugammadex treatment group, and 1/68 (1.5%) in the 16 mg/kg sugammadex treatment group, compared to 1/51 (2.0%) in the neostigmine + glycopyrrolate treatment group. The adverse reaction profiles in ASA Class 3 and 4 patients were generally similar to those in adult patients in pooled Phase 1 to 3 studies; therefore, no dosage adjustment is necessary [see Dosage and Administration (2.1), Adverse Reactions (6.1)] .

10 OVERDOSAGE

In premarketing clinical trials, one case of accidental overdose with 40 mg/kg BRIDION was reported without significant effects.

BRIDION can be removed using hemodialysis with a high-flux filter, but not with a low-flux filter. Based upon clinical studies, BRIDION concentrations in plasma are reduced with a high-flux filter by about 70% after a 3- to 6-hour dialysis session.

11 DESCRIPTION

BRIDION (sugammadex) injection, for intravenous use, contains sugammadex sodium, a modified gamma cyclodextrin chemically designated as 6A,6B,6C,6D,6E,6F,6G,6H-Octakis-S-(2-carboxyethyl)-6A,6B,6C,6D,6E,6F,6G,6H-octathio- γ-cyclodextrin sodium salt(1:8) with a molecular weight of 2178.01. The structural formula is:

BRIDION is supplied as a sterile, non-pyrogenic aqueous solution that is clear, colorless to slightly yellow-brown for intravenous injection only. Each mL contains 100 mg sugammadex, which is equivalent to 108.8 mg sugammadex sodium. The aqueous solution is adjusted to a pH of between 7 and 8 with hydrochloric acid and/or sodium hydroxide. The osmolality of the product is between 300 and 500 mOsmol/kg.

BRIDION may contain up to 7 mg/mL of the mono OH-derivative of sugammadex [see Clinical Pharmacology (12.2)] . This derivative is chemically designated as 6A,6B,6C,6D,6E,6F,6G-Heptakis-S-(2-carboxyethyl)-6A,6B,6C,6D,6E,6F,6G-heptathio- γ-cyclodextrin sodiumsalt (1:7) with a molecular weight of 2067.90. The structural formula is:

12 CLINICAL PHARMACOLOGY

12.1 Mechanism of Action

BRIDION is a modified gamma cyclodextrin. It forms a complex with the neuromuscular blocking agents rocuronium and vecuronium, and it reduces the amount of neuromuscular blocking agent available to bind to nicotinic cholinergic receptors in the neuromuscular junction. This results in the reversal of neuromuscular blockade induced by rocuronium and vecuronium.

12.2 Pharmacodynamics

BRIDION has been administered in doses ranging from 0.5 mg/kg to 16 mg/kg in dose response trials of rocuronium-induced blockade (0.6, 0.9, 1 and 1.2 mg/kg with and without maintenance doses) and vecuronium-induced blockade (0.1 mg/kg with or without maintenance doses) at different time points/depths of block. In these trials a clear dose-response relationship was observed.

BRIDION may contain up to 7% of the mono OH-derivative of sugammadex. In preclinical pharmacology studies, the mono OH-derivative was demonstrated to have ~50% of the affinity as sugammadex for rocuronium and vecuronium and that product with up to 7% of the mono OH-derivative has nearly similar efficacy in reversing rocuronium- or vecuronium-induced blockade.

Although sugammadex has greatest affinity for aminosteroid neuromuscular blocking agents such as rocuronium and vecuronium, plasma levels of endogenous or exogenous compounds with a similar steroidal structure, such as some hormones, hormonal contraceptives, and pheromones may also be reduced following administration of sugammadex [see Drug Interactions (7.3)] .

Cardiac Electrophysiology

At a dose 2 times the maximum recommended dose, sugammadex does not prolong the QTc interval to any clinically relevant extent.

12.3 Pharmacokinetics

The sugammadex pharmacokinetic parameters were calculated from the total sum of non-complex-bound and complex-bound concentrations of sugammadex. Pharmacokinetic parameters as clearance and volume of distribution are assumed to be the same for non-complex-bound and complex-bound sugammadex in anesthetized patients.

Distribution

The observed steady-state volume of distribution of sugammadex is approximately 11 to 14 liters in adult patients with normal renal function (based on conventional, non-compartmental pharmacokinetic analysis). Neither sugammadex nor the complex of sugammadex and rocuronium binds to plasma proteins or erythrocytes, as was shown in vitrousing male human plasma and whole blood. Sugammadex exhibits linear kinetics in the dosage range of 1 to 16 mg/kg when administered as an IV bolus dose.

In nonclinical drug distribution studies, sugammadex is retained in sites of active mineralization, such as bone and teeth, with a mean half-life of 172 and 8 days, respectively [see Use in Specific Populations (8.4), Nonclinical Toxicology (13.2)] .

Metabolism

In clinical studies, no metabolites of sugammadex have been observed and only renal excretion of the unchanged product was observed as the route of elimination.

Elimination

In adult anesthetized patients with normal renal function, the elimination half-life (t1/2) of sugammadex is about 2 hours and the estimated plasma clearance is about 88 mL/min (based on compartmental pharmacokinetic analysis). A mass balance study demonstrated that >90% of the dose was excreted within 24 hours. Ninety-six percent (96%) of the dose was excreted in urine, of which at least 95% could be attributed to unchanged sugammadex. Excretion via feces or expired air was less than 0.02% of the dose. Administration of BRIDION to healthy volunteers resulted in increased renal elimination of rocuronium in complex.

Patients with Renal Impairment

Sugammadex is known to be substantially excreted by the kidney. The half-life of sugammadex in patients with mild, moderate and severe renal impairment is 4, 6, and 19 hours, respectively.

In one study, exposure to sugammadex was prolonged, leading to 17-fold higher overall exposure in patients with severe renal impairment. Low concentrations of sugammadex are detectable for at least 48 hours post-dose in patients with severe renal impairment.

In a second study comparing subjects with moderate or severe renal impairment to subjects with normal renal function, sugammadex clearance progressively decreased and t1/2was progressively prolonged with declining renal function. Exposure was 2-fold and 5-fold higher in subjects with moderate and severe renal impairment, respectively. Sugammadex concentrations were no longer detectable beyond 7 days post-dose in subjects with severe renal impairment.

Geriatric Patients

Geriatric patients may have mild or moderate renal impairment. Population pharmacokinetic analysis indicated that, beyond the effects of a decreased creatinine clearance, increased age has limited impact on sugammadex PK parameters [see Use in Specific Populations (8.5, 8.6)].

Pediatric Patients

The pharmacokinetics of sugammadex in pediatric patients have been evaluated in 2 clinical studies following administration of intravenous doses of 2 or 4 mg/kg sugammadex administered for reversal of moderate or deep neuromuscular blockade, respectively. In one study, sugammadex pharmacokinetic parameters were estimated in pediatric patients 2 to <17 years of age with patients enrolled into 3 age groups (2 to <6, 6 to <12 and 12 to <17 years of age). In a second study, sugammadex pharmacokinetic parameters were estimated in pediatric patients birth to <2 years of age with patients enrolled into 4 age groups (birth to 27 days, 28 days to <3 months, 3 months to <6 months and 6 months to < 2 years).

Sugammadex exposure (AUC0-infand Cmax) increased in a dose-dependent, linear manner following administration of 2 or 4 mg/kg across patients birth to <17 years of age. Sugammadex exposure was approximately 40% lower in patients <6 years of age following administration of 2 or 4 mg/kg sugammadex compared to older pediatric patients (6 to <17 years) and adults; however, this difference was not clinically relevant [see Clinical Studies (14.1)] .

Both clearance and volume of distribution increase with increasing age in pediatric patients, whereas elimination half-life is generally similar across pediatric patients. As a result, the observed steady-state volume of distribution of sugammadex is approximately 3 to 10 liters and clearance is approximately 38 to 95 mL/min resulting in a half-life of approximately 1-2 hours in pediatric patients 2 to <17 years of age. By comparison, observed steady-state volume of distribution of sugammadex is approximately 1 to 3 liters and clearance is approximately 38 to 95 mL/min with a half-life of approximately 1-2 hours in pediatric patients birth to <2 years of age.

Sex

No pharmacokinetic differences between male and female subjects were observed.

Race

In a study in healthy Japanese and Caucasian subjects no clinically relevant differences in pharmacokinetic parameters were observed. Limited data do not indicate differences in pharmacokinetic parameters in Black or African Americans.

Obesity

In one clinical study of obese patients with a body mass index ≥40 kg/m^2, sugammadex 2 mg/kg and 4 mg/kg was dosed according to ABW (n=76) or IBW (n=74). Sugammadex exposure increased in a dose-dependent, linear manner following administration according to ABW or IBW. No clinically relevant differences in pharmacokinetic parameters were observed between obese patients and the general population, when dosed according to ABW. [See Use in Specific Populations (8.10).] Systemic exposure of sugammadex is approximately 50% lower with IBW dosing compared to ABW.

13 NONCLINICAL TOXICOLOGY

13.1 Carcinogenesis, Mutagenesis, Impairment of Fertility

Carcinogenesis

Long-term animal studies to evaluate the carcinogenic potential of sugammadex have not been conducted.

Mutagenesis

Sugammadex and its mono OH-derivative tested negatively in in vitrobacterial reverse mutation assays (Ames test), in vitrochromosomal aberration assays in human peripheral blood lymphocytes, and in vivomicronucleus assays in mice and rats.

Impairment of Fertility

A fertility and early embryonic development study in Sprague-Dawley rats in which male rats were treated daily for 29 days prior to mating and through the mating period and female rats were treated daily for 14 days prior to mating to Day 5 post-coitum via intravenous administration of sugammadex at 20, 100, and 500 mg/kg (0.2, 1, and 6 times the MRHD of 16 mg/kg, respectively, based on AUC comparison) did not show adverse effects on fertility.

13.2 Animal Toxicology and/or Pharmacology

Bone and teeth retention of sugammadex occurred in rats after intravenous injection, with mean half-lives of 172 and 8 days, respectively. Sugammadex bound to hydroxyapatite in an in vitrostudy and distributed in the bone formation area where hydroxyapatite is present for mineralization in vivo.

In adult rat bone toxicity studies, a single dose of sugammadex at 2000 mg/kg (approximately 24 times the maximum recommended human dose (MRHD) of 16 mg/kg by AUC comparison) administered to adult rats caused a slight increase in bone resorption, but had no effect on teeth color. No adverse bone effects were seen following a single dose of sugammadex at 500 mg/kg (4 times the MRHD dose of 16 mg/kg based on plasma AUC comparison).

In a bone repair study, adult rats were treated with intravenous sugammadex weekly for 6 weeks at 0, 30, 120, and 500 mg/kg (approximately 0.4, 1, and 6 times the MRHD, respectively, by AUC comparison). Based on histological data, high dose animals with post-fracture treatment, showed a statistically significant increase in callus formation and decrease in bone formation, suggesting a potential for a slight delay in the bone healing process. However, there were no statistically significant effects on bone volume or bone mineral density.

In juvenile animal studies, bone and teeth deposition was significantly higher in juvenile rats compared to adults. In addition, sugammadex administered to juvenile rats daily for 4 weeks caused slight bone length decrease (approximately 3%), which did not recover after an 8-week treatment-free period, and reversible whitish discoloration of the teeth at a dose approximately 0.6 times the MRHD, while weekly administration for 8 weeks did not produce similar changes in bone and teeth at doses up to 1.2 times the MRHD [see Use in Specific Populations (8.4)] .

14 CLINICAL STUDIES

14.1 Controlled Clinical Studies

Comparative Study of BRIDION versus Neostigmine as a Reversal Agent for Neuromuscular Blockade Induced by Rocuronium or Vecuronium at Reappearance of T2(Moderate Blockade)

A multicenter, randomized, parallel-group, active-controlled, safety-assessor blinded study comparing BRIDION and neostigmine enrolled 189 patients (87 women and 102 men, 95% were ASA class 1 and 2 and 99% were Caucasian, median weights were 72 kg and 76 kg and median ages were 50 years and 51 years in the rocuronium and vecuronium groups, respectively). Patients were randomly assigned to the rocuronium or vecuronium group and underwent elective surgical procedures under general anesthesia that required endotracheal intubation and maintenance of neuromuscular blockade. The surgical procedures were mainly endocrine, ocular, ENT, abdominal (gynecological, colorectal, urological), orthopedic, vascular, or dermatological. At the reappearance of T2, after the last dose of rocuronium or vecuronium, 2 mg/kg BRIDION or 50 mcg/kg neostigmine was administered in a randomized order as a single bolus injection. The time from start of administration of BRIDION or neostigmine to recovery of the TOF (T4/T1) ratio to 0.9 was assessed. Generally, a T4/T1ratio ≥0.9 correlates with recovery from neuromuscular blockade.

Return of the T4/T1ratio to 0.9 after the reappearance of T2was overall faster with BRIDION 2 mg/kg as compared to neostigmine 50 mcg/kg in the setting of rocuronium or vecuronium-induced neuromuscular blockade (Figures 1 and 2).

Figure 1: Time (Minutes) from Administration of BRIDION or Neostigmine at the Reappearance of T2after Rocuronium to Recovery of the T4/T1Ratio to 0.9

Figure 2: Time (Minutes) from Administration of BRIDION or Neostigmine at the Reappearance of T2after Vecuronium to Recovery of the T4/T1Ratio to 0.9

Comparative Study of BRIDION versus Neostigmine as a Reversal Agent for Neuromuscular Blockade Induced by Rocuronium or Vecuronium at 1 to 2 PTCs (Deep Blockade)

A multicenter, randomized, parallel-group, active-controlled, safety-assessor blinded study comparing BRIDION and neostigmine enrolled 157 patients (86 women and 71 men; 8% ASA class 1, 71% class 2, and 21% class 3; 79% Caucasian; median weights of 81 kg and 84 kg, and median ages of 54 years and 56 years in the rocuronium and vecuronium groups, respectively). Patients were randomly assigned to the rocuronium or vecuronium group and underwent elective surgical procedures under general anesthesia that required endotracheal intubation and maintenance of neuromuscular blockade. The surgical procedures were mainly abdominal (gynecological, colorectal, urological), orthopedic, reconstructive, or neurological. At 1 to 2 PTCs, after the last dose of rocuronium or vecuronium, 4 mg/kg BRIDION or 70 mcg/kg neostigmine was administered in a randomized order as a single bolus injection. The time from start of administration of BRIDION or neostigmine to recovery of the TOF (T4/T1) ratio to 0.9 was assessed, although neostigmine was not expected to reverse neuromuscular blockade at a depth of 1 to 2 PTCs. Generally, a T4/T1ratio ≥0.9 correlates with recovery from neuromuscular blockade.

Return of the T4/T1ratio to 0.9 in patients with 1 to 2 PTCs with BRIDION 4 mg/kg had a wider range of recovery times but the median time to recovery was comparable to the study of reversal at T2(2.7 minutes with 25thand 75thpercentiles of 2.1 and 4.3 minutes for rocuronium [N=37], and 3.3 minutes with 25thand 75thpercentiles of 2.3 and 6.6 minutes for vecuronium [N=47]). There were 7 and 6 censored observations in the rocuronium and vecuronium groups, respectively.

Reversal of Neuromuscular Blockade 3 Minutes after Rocuronium 1.2 mg/kg

Time to recovery from neuromuscular blockade induced by succinylcholine compared with recovery from neuromuscular blockade induced by rocuronium followed 3 minutes later with BRIDION was assessed in a multicenter, randomized, parallel-group, active-controlled, safety-assessor blinded study. The study was conducted in 110 patients (64 women and 46 men, ASA class 1 and 2, 78% were Caucasian, median weight was 70 kg, median age was 43 years). Patients underwent elective surgical procedures under general anesthesia that required endotracheal intubation and a short duration of neuromuscular relaxation. The laparoscopic or open surgical procedures were mainly gynecological, orthopedic, or reconstructive. Return of the first twitch in a TOF (T1) to 10% of baseline was compared between BRIDION 16 mg/kg for reversal of rocuronium 1.2 mg/kg versus spontaneous recovery from succinylcholine 1 mg/kg.

Recovery to T1of 10% of baseline (relative to the time of administration of rocuronium or succinylcholine) was overall faster in the rocuronium/BRIDION group compared with succinylcholine alone (Table 5).

Table 5: Time (minutes) from Start of Administration of Rocuronium or Succinylcholine to Recovery of T1to 10% of Baseline
 | Treatment Regimen
 | Rocuronium (1.2 mg/kg) and BRIDION (16 mg/kg) | Succinylcholine (1 mg/kg)
N | 55 | 55
Mean (SD) | 4.4 (0.7) | 7.1 (1.6)
Median (Range) | 4.2 (3.5 – 7.7) | 7.1 (3.8 – 10.5)

Comparative Studies of BRIDION versus Neostigmine as a Reversal Agent for Neuromuscular Blockade Induced by Rocuronium or Vecuronium in Pediatric Patients

2 to <17 Years of Age

Time to recovery from neuromuscular blockade induced by rocuronium or vecuronium followed by administration of BRIDION or neostigmine was assessed in a randomized, double-blind, active comparator-controlled study. The study was conducted in 288 randomized pediatric patients 2 to <17 years of age, of which 276 patients received treatment (153 boys and 123 girls; ASA class 1, 2, and 3; 89.5% were Caucasian; median weight was 25 kg; median age was 7 years). The primary efficacy objective was to evaluate the effect of BRIDION compared to neostigmine for reversal of moderate neuromuscular blockade as measured by time to recovery to a TOF ratio of ≥0.9.

Recovery to a TOF ratio of ≥0.9 was statistically significantly faster in pediatric patients 2 to <17 years of age dosed with BRIDION 2 mg/kg (N=33) compared with neostigmine (N=34) for reversal of moderate block based on a geometric mean of 1.7 minutes for BRIDION 2 mg/kg and 7.4 minutes for neostigmine (ratio of geometric means was 0.22, 95% CI (0.16, 0.32)). These effects were consistent across age cohorts studied (2 to <6; 6 to <12; 12 to <17 years of age) and neuromuscular blocking agent (rocuronium and vecuronium).

Birth to <2 Years of Age

Time to recovery from neuromuscular blockade induced by rocuronium or vecuronium followed by administration of BRIDION or neostigmine was assessed in a randomized, double-blind, active comparator-controlled study. The study was conducted in 145 randomized pediatric patients from birth to <2 years of age, of which 138 patients received treatment (92 boys and 46 girls; ASA class 1, 2, and 3; 68% were White; median weight was 5.8 kg; median age was 100.5 days). The primary efficacy objective was to evaluate the time to neuromuscular recovery of BRIDION in comparison to neostigmine for the reversal of moderate neuromuscular blockade.

Time to neuromuscular recovery was statistically significantly faster in participants dosed with BRIDION 2 mg/kg (N=29) compared with neostigmine (N=31) (median of 1.4 minutes for BRIDION 2 mg/kg and 4.4 minutes for neostigmine; hazard ratio=2.40, 95% CI: 1.37, 4.18). BRIDION 4 mg/kg achieved neuromuscular recovery with a median of 1.1 minutes. These effects were consistent across age cohorts studied (birth to 27 days, 28 days to <3 months, 3 months to <6 months, 6 months to <2 years of age).

16 HOW SUPPLIED/STORAGE AND HANDLING

BRIDION (sugammadex) injection is a clear, colorless to slightly yellow-brown, non-pyrogenic aqueous solution intended for intravenous infusion. BRIDION is available in the following presentations:

- BRIDION 2-mL single-dose vial containing 200 mg sugammadex (100 mg/mL)
  NDC 84549-423-12

The packaging of this product is not made with natural rubber latex.

STORAGE AND HANDLING

Store at 25°C (77°F); excursions permitted to 15°C to 30°C (59°F to 86°F) (see USP Controlled Room Temperature). Protect from light. When not protected from light, the vial should be used within 5 days.

Discard unused portion.

17 PATIENT COUNSELING INFORMATION

- Advise females of reproductive potential using hormonal contraceptives that BRIDION may reduce the contraceptive effect .Instruct females to use an additional, non-hormonal method of contraception for the next 7 days following BRIDION administration [see Drug Interactions (7.3)].

Distributed by: Merck Sharp & Dohme LLC
Rahway, NJ 07065, USA

For patent information: www.msd.com/research/patent

Copyright © 2015-2024 Merck & Co., Inc., Rahway, NJ, USA, and its affiliates.
All rights reserved.

uspi-mk8616-soi-2412r010